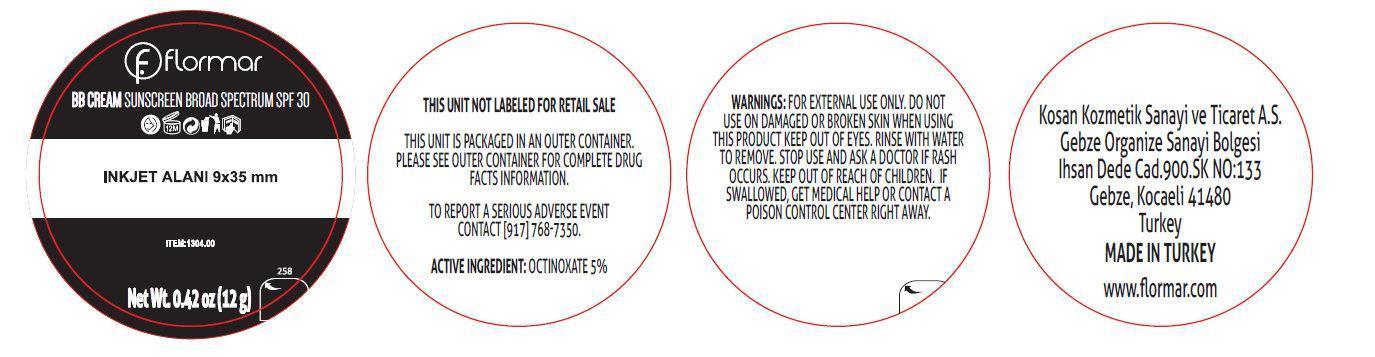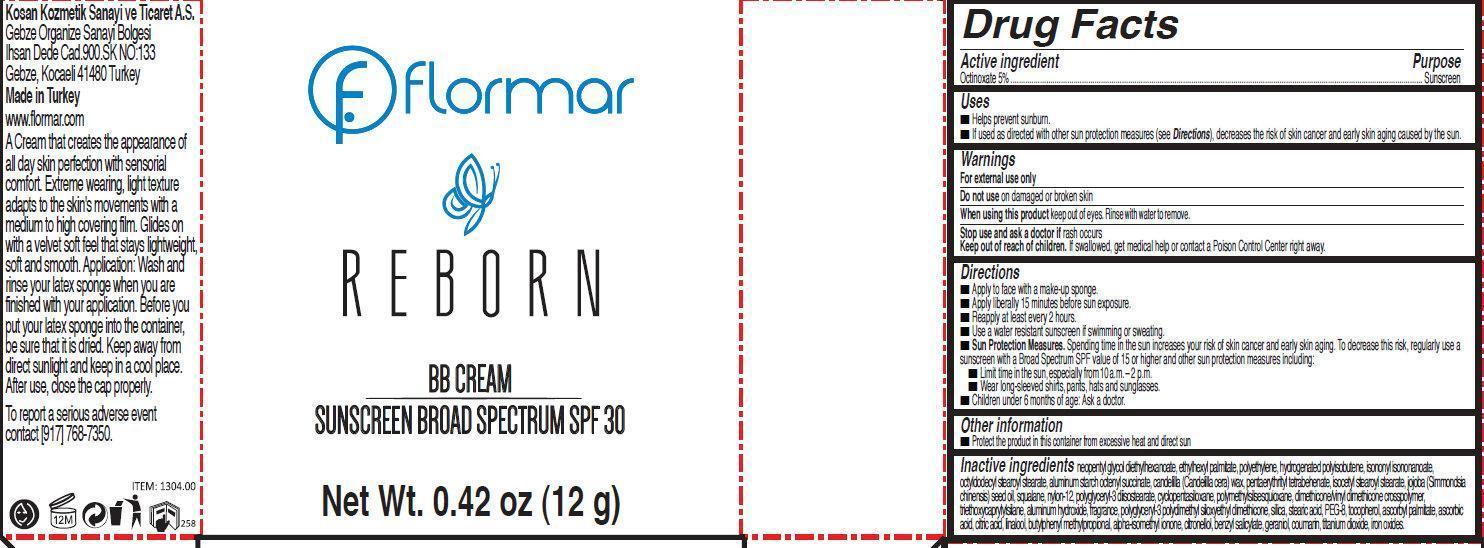 DRUG LABEL: flormar REBORN BB SUNSCREEN BROAD SPECTRUM SPF 30 CP24 Medium
NDC: 61722-168 | Form: CREAM
Manufacturer: Kosan Kozmetik Sanayi ve Ticaret A.S.
Category: otc | Type: HUMAN OTC DRUG LABEL
Date: 20191018

ACTIVE INGREDIENTS: OCTINOXATE 5 g/100 g
INACTIVE INGREDIENTS: NEOPENTYL GLYCOL DIETHYLHEXANOATE; ETHYLHEXYL PALMITATE; HIGH DENSITY POLYETHYLENE; ISONONYL ISONONANOATE; OCTYLDODECYL STEAROYL STEARATE; ALUMINUM STARCH OCTENYLSUCCINATE; CANDELILLA WAX; PENTAERYTHRITYL TETRABEHENATE; ISOCETYL STEAROYL STEARATE; JOJOBA OIL; SQUALANE; NYLON-12; POLYGLYCERYL-3 DIISOSTEARATE; CYCLOMETHICONE 5; ALUMINUM HYDROXIDE; SILICON DIOXIDE; STEARIC ACID; POLYETHYLENE GLYCOL 400; TOCOPHEROL; ASCORBYL PALMITATE; ASCORBIC ACID; CITRIC ACID MONOHYDRATE; LINALOOL, (+/-)-; BUTYLPHENYL METHYLPROPIONAL; ISOMETHYL-.ALPHA.-IONONE; .BETA.-CITRONELLOL, (R)-; BENZYL SALICYLATE; GERANIOL; COUMARIN; TITANIUM DIOXIDE; FERRIC OXIDE RED

flormar REBORN BB CREAM SUNSCREEN BROAD SPECTRUM SPF 30 CP24 Medium

Active ingredient

Octinoxate 5%

Purpose

Sunscreen

Uses

- Helps prevent sunburn.
- If used as directed with other sun protection measures (see Directions), decreases the risk of skin cancer and early skin aging caused by the sun.

Warnings

For external use only

Do not use

on damaged or brokenskin

When using this product

keep out of eyes. Rinse with water to remove.

Stop use and ask a doctor if

rash occurs

Keep out of reach of children.

If swallowed, get medical help or contact a Poison Control Center right away.

Directions

- Apply to face with a make-up sponge.
- Apply liberally 15 minutes before sun exposure.
- Reapply at least every 2 hours.
- Use a water resistant sunscreen if swimming or sweating.
- Sun Protection Measures. Spending time in the sun increases your risk of skin cancer and early skin aging. To decrease this risk, regularly use a sunscreen with a Broad Spectrum SPF value of 15 or higher and other sun protection measures including:
-
  - Limit time in the sun, especially from 10 a.m. – 2 p.m.
  - Wear long-sleeved shirts, pants, hats and sunglasses.
- Children under 6 months of age: Ask a doctor.

Other information

- Protect the product in this container from excessive heat and direct sun

Inactive ingredients

neopentyl glycol diethylhexanoate, ethylhexyl palmitate, polyethylene, hydrogenated polyisobutene, isononyl isononanoate, octyldodecyl stearoyl stearate, aluminum starch octenyl succinate, candelilla (Candelilla cera) wax, pentaerythrityl tetrabehenate, isocetyl stearoyl stearate, jojoba (Simmondsia chinensis) seed oil, squalane, nylon-12, polyglyceryl-3 diisostearate, cyclopentasiloxane, polymethylsilsesquioxane, dimethicone/vinyl dimethicone crosspolymer, triethoxycaprylylsilane, aluminum hydroxide, fragrance, polyglyceryl-3 polydimethyl siloxyethyl dimethicone, silica, stearic acid, PEG-8, tocopherol, ascorbyl palmitate, ascorbic acid, citric acid, linalool, butylphenyl methylpropional, alpha-isomethyl ionone, citronellol, benzyl salicylate, geraniol, coumarin, titanium dioxide, iron oxides

Product Labels

Enter section text here